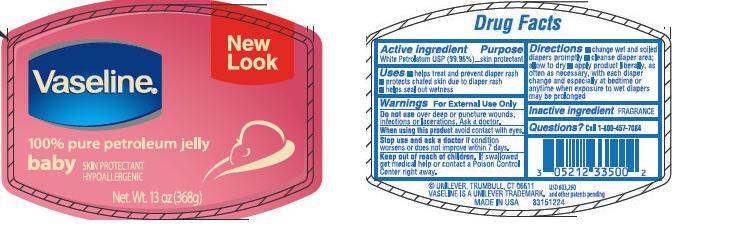 DRUG LABEL: Vaseline
NDC: 64942-0016 | Form: JELLY
Manufacturer: Conopco Inc. d/b/a Unilever
Category: otc | Type: HUMAN OTC DRUG LABEL
Date: 20120425

ACTIVE INGREDIENTS: petrolatum 99.96 g/100 g

Vaseline Pure Petroleum Jelly Baby PDP and drug facts

Active ingredient
WHITE PETROLATUM, USP (99.96%)

Purpose
skin protectant

Uses
￭ helps treat and prevent diaper rash
￭ protects chafed skin due to diaper rash
￭ helps seal out wetness

Warnings
For External Use Only

Do not use over deep or puncture wounds, infections or lacerations. Ask a doctor.

When using this product do not get into eyes

Stop use and ask a doctor if condition worsens or does not improve within 7 days.

Keep out of reach of children. If swallowed get medical help or contact a Poison Control Center right away.

Directions
￭ change wet and soiled diapers promptly
￭ cleanse diaper area; allow to dry
￭ apply product liberally, as often as necessary, with each diaper change and especially at bedtime or anytime when exposure to wet diapers may be prolonged

Inactive ingredient FRAGRANCE

Questions? Call 1-800-457-7084

PACKAGE LABEL

VPJ Baby 13 oz PDP